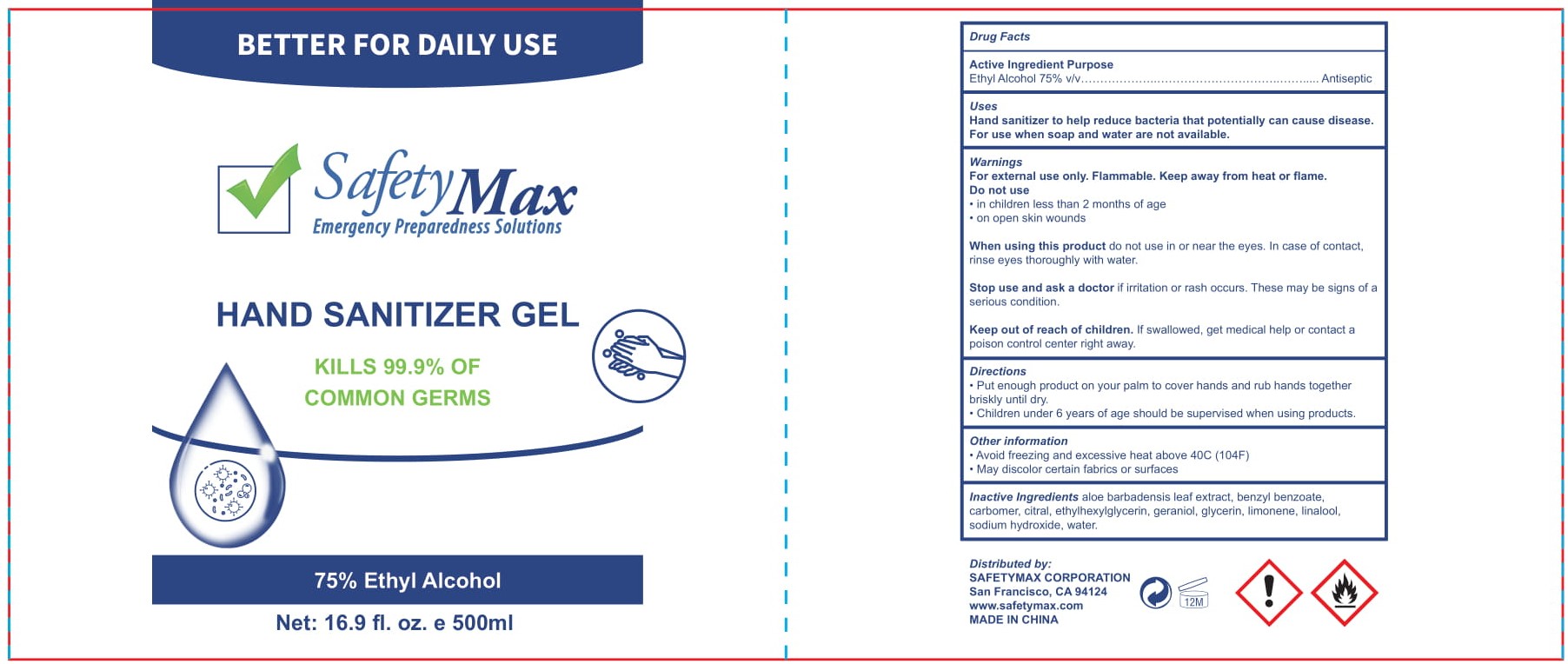 DRUG LABEL: Safety Max
NDC: 78503-111 | Form: GEL
Manufacturer: SafetyMax Corporation
Category: otc | Type: HUMAN OTC DRUG LABEL
Date: 20200701

ACTIVE INGREDIENTS: ALCOHOL 75 mL/100 mL
INACTIVE INGREDIENTS: ALOE VERA LEAF; GERANIOL; CITRAL; LINALOOL, (+)-; GLYCERIN; CARBOMER 934; WATER; BENZYL ALCOHOL; SODIUM HYDROXIDE; BENZYL BENZOATE; LIMONENE, (+)-; ETHYLHEXYLGLYCERIN

SafetyMax Sanitizer Gel

Active Ingredient(s)

Alcohol 75% v/v. Purpose: Antiseptic

Purpose

Antiseptic, Hand Sanitizer

Use

To decrease bacteria on the skin that could cause disease. Recommended for repeated use.

Warnings

Flammable. Keep away from heat or flame.

For external use only-Hands.

When using this product keep out of eyes, ears, and mouth. In case of contact with eyes, rinse eyes thoroughly with water.
Stop use and ask a doctor if irritation or rash occurs. These may be signs of a serious condition.
Keep out of reach of children. If swallowed, get medical help or contact a Poison Control Center right away.

Stop use and ask a doctor if irritation or rash occurs. These may be signs of a serious condition.

Keep out of reach of children. If swallowed, get medical help or contact a Poison Control Center right away.

Directions

- Wet hands thoroughly with product and allow to dry without whipping.
- For children under 6 years use only under adult supervision.
- Not recommended for infants.

Other information

- Store below 106 F (41 C)
- May discolor certain fabrics or surfaces.

Inactive ingredients

Water, glycerin, carbomer, sodium hydroxide, Ethylhexyl glycerin, Aloe barbadensis leaf extract

Package Label - Principal Display Panel

500 mL NDC: 78503-111-03